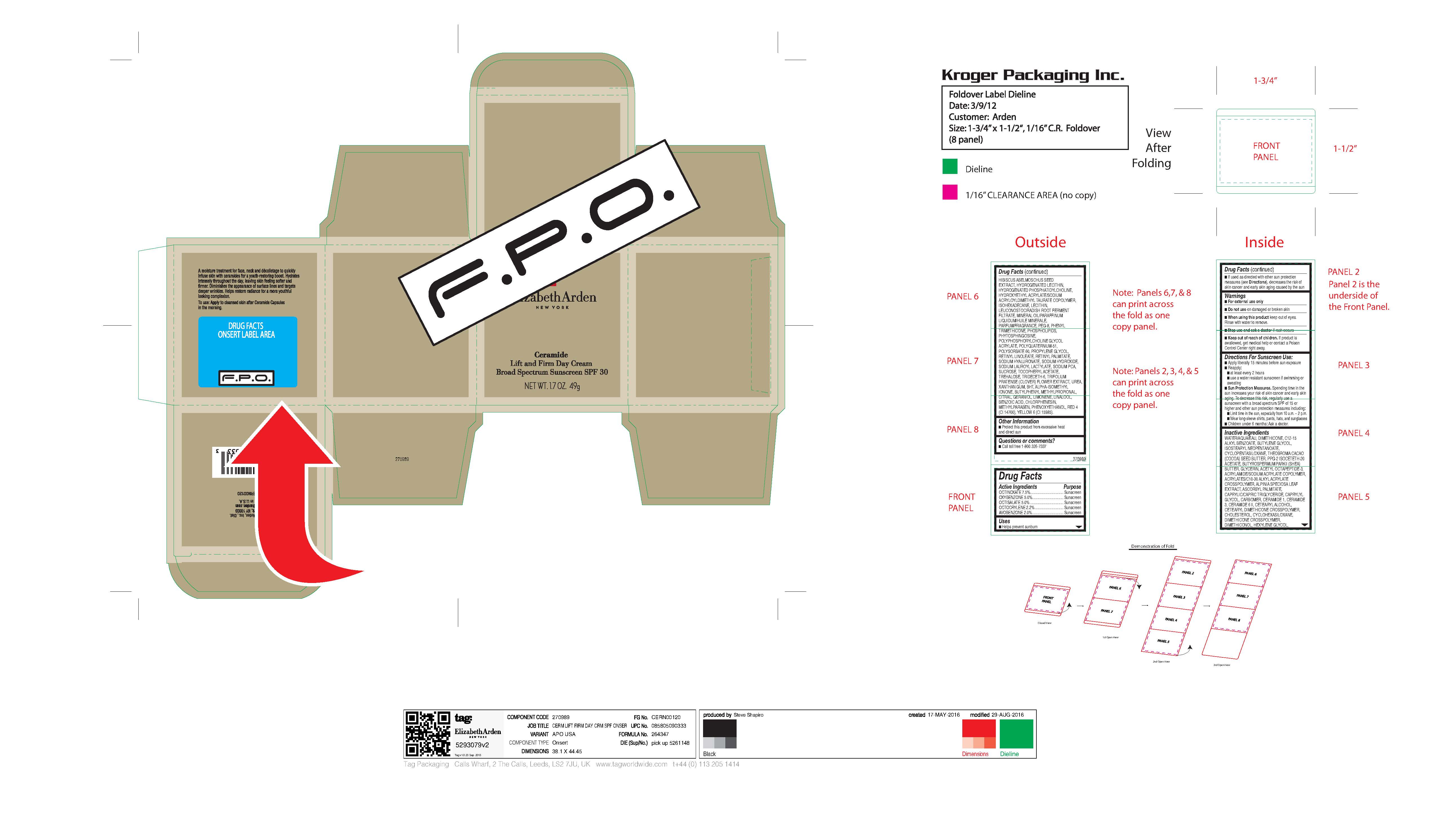 DRUG LABEL: CERAMIDE LIFT and FIRM
NDC: 10967-666 | Form: EMULSION
Manufacturer: REVLON
Category: otc | Type: HUMAN OTC DRUG LABEL
Date: 20240112

ACTIVE INGREDIENTS: OXYBENZONE 5 mg/1 g; OCTISALATE 5 mg/1 g; OCTINOXATE 7.5 mg/1 g; OCTOCRYLENE 2.2 mg/1 g
INACTIVE INGREDIENTS: SUCROSE; ACETYL OCTAPEPTIDE-3; CETOSTEARYL ALCOHOL; ALKYL (C12-15) BENZOATE; ISOSTEARYL NEOPENTANOATE; WATER; DIMETHICONE; .ALPHA.-TOCOPHEROL ACETATE; TRIFOLIUM PRATENSE FLOWER; CERAMIDE 6 II; CERAMIDE 3; CYCLOMETHICONE 5; BUTYLENE GLYCOL; VITAMIN A PALMITATE; ISOMETHYL-.ALPHA.-IONONE; COCOA BUTTER; PPG-2 ISOCETETH-20 ACETATE; EGG PHOSPHOLIPIDS; BUTYLPHENYL METHYLPROPIONAL; CITRAL; CERAMIDE 1; POLYETHYLENE GLYCOL 400; CARBOMER INTERPOLYMER TYPE A (ALLYL SUCROSE CROSSLINKED); CHOLESTEROL; ASCORBYL PALMITATE; XANTHAN GUM; METHYLPARABEN; BUTYROSPERMUM PARKII (SHEA) BUTTER UNSAPONIFIABLES; GLYCERIN; HEXYLENE GLYCOL; ABELMOSCHUS MOSCHATUS SEED; HYDROGENATED SOYBEAN LECITHIN; LEUCONOSTOC/RADISH ROOT FERMENT FILTRATE; LECITHIN, SOYBEAN; MINERAL OIL; PHYTOSPHINGOSINE; LIMONENE, (+)-; HYDROXYETHYL ACRYLATE/SODIUM ACRYLOYLDIMETHYL TAURATE COPOLYMER (45000 MPA.S AT 1%); ALPINIA ZERUMBET LEAF; CAPRYLYL GLYCOL; CARBOMER HOMOPOLYMER, UNSPECIFIED TYPE; DIMETHICONE CROSSPOLYMER (450000 MPA.S AT 12% IN CYCLOPENTASILOXANE); ISOHEXADECANE; UREA; PHENOXYETHANOL; RETINYL LINOLEATE; HYALURONATE SODIUM; SODIUM HYDROXIDE; BENZOIC ACID; PROPYLENE GLYCOL; CYCLOMETHICONE 6; BUTYLATED HYDROXYTOLUENE; LINALOOL, (+/-)-; FD&C YELLOW NO. 6; SODIUM LAUROYL LACTYLATE; SODIUM PYRROLIDONE CARBOXYLATE; POLYQUATERNIUM-51 (2-METHACRYLOYLOXYETHYL PHOSPHORYLCHOLINE/N-BUTYL METHACRYLATE; 4:1); POLYSORBATE 60; MEDIUM-CHAIN TRIGLYCERIDES; GERANIOL; PHENYL TRIMETHICONE; TREHALOSE; FD&C RED NO. 4; CHLORPHENESIN; TRIDECETH-6

CERAMIDE LIFT AND FIRM DAY CREAM BROAD SPECTRUM SUNSCREEN SPF 30

ACTIVE INGREDIENTS

OCTINOXATE 7.5%.................................. Sunscreen
OXYBENZONE 5.0%................................ Sunscreen
OCTISALATE 5.0% .................................. Sunscreen
OCTOCRYLENE 2.2% ............................. Sunscreen
AVOBENZONE 2.0%................................ Sunscreen

USES

■ Helps prevent sunburn
■ If used as directed with other sun protection measures (see Directions), decreases the risk of skin cancer and early skin aging caused by the sun

WARNINGS

■ For external use only
■ Do not use on damaged or broken skin
■ When using this product keep out of eyes. Rinse with water to remove.
■ Stop use and ask a doctor if rash occurs
■ Keep out of reach of children. If product is swallowed, get medical help or contact a Poison Control Center right away.

DIRECTIONS FOR SUNSCREEN USE

■ Apply liberally 15 minutes before sun exposure
■ Reapply:
■ at least every 2 hours
■ use a water resistant sunscreen if swimming or sweating
■ Sun Protection Measures. Spending time in the
sun increases your risk of skin cancer and early skin
aging. To decrease this risk, regularly use a
sunscreen with a broad spectrum SPF of 15 or
higher and other sun protection measures including:
■ Limit time in the sun, especially from 10 a.m. – 2 p.m.
■ Wear long-sleeve shirts, pants, hats, and sunglasses
■ Children under 6 months: Ask a doctor.

OTHER INGREDIENTS

WATER/AQUA/EAU, DIMETHICONE, C12-15 ALKYL BENZOATE, BUTYLENE GLYCOL, ISOSTEARYL NEOPENTANOATE, CYCLOPENTASILOXANE, THEOBROMA CACAO (COCOA) SEED BUTTER, PPG-2 ISOCETETH-20 ACETATE, BUTYROSPERMUM PARKII (SHEA) BUTTER, GLYCERIN, ACETYL OCTAPEPTIDE-3, ACRYLAMIDE/SODIUM ACRYLATE COPOLYMER, ACRYLATES/C10-30 ALKYL ACRYLATE CROSSPOLYMER, ALPINIA SPECIOSA LEAF EXTRACT, ASCORBYL PALMITATE, CAPRYLIC/CAPRIC TRIGLYCERIDE, CAPRYLYL GLYCOL, CARBOMER, CERAMIDE 1, CERAMIDE 3, CERAMIDE 6 II, CETEARYL ALCOHOL, CETEARYL DIMETHICONE CROSSPOLYMER, CHOLESTEROL, CYCLOHEXASILOXANE, DIMETHICONE CROSSPOLYMER, DIMETHICONOL, HEXYLENE GLYCOL, HIBISCUS ABELMOSCHUS SEED EXTRACT, HYDROGENATED LECITHIN, HYDROGENATED PHOSPHATIDYLCHOLINE, HYDROXYETHYL ACRYLATE/SODIUM ACRYLOYLDIMETHYL TAURATE COPOLYMER, ISOHEXADECANE, LECITHIN, LEUCONOSTOC/RADISH ROOT FERMENT FILTRATE, MINERAL OIL/PARAFFINUM LIQUIDUM/HUILE MINERALE, PARFUM/FRAGRANCE, PEG-8, PHENYL TRIMETHICONE, PHOSPHOLIPIDS, PHYTOSPHINGOSINE, POLYPHOSPHORYLCHOLINE GLYCOL ACRYLATE, POLYQUATERNIUM-51, POLYSORBATE 60, PROPYLENE GLYCOL, RETINYL LINOLEATE, RETINYL PALMITATE, SODIUM HYALURONATE, SODIUM HYDROXIDE, SODIUM LAUROYL LACTYLATE, SODIUM PCA, SUCROSE, TOCOPHERYL ACETATE, TREHALOSE, TRIDECETH-6, TRIFOLIUM PRATENSE (CLOVER) FLOWER EXTRACT, UREA, XANTHAN GUM, BHT, ALPHA-ISOMETHYL IONONE, BUTYLPHENYL METHYLPROPIONAL, CITRAL, GERANIOL, LIMONENE, LINALOOL, BENZOIC ACID, CHLORPHENESIN, METHYLPARABEN, PHENOXYETHANOL, RED 4 (CI 14700), YELLOW 6 (CI 15985).

DOSAGE AND ADMINISTRATION

As needed

Warnings

- For external use only
- Do not use on damage or broken skin
- When using this product keep out of eyes. Rinse with water to remove.
- Stop use and ask a doctor if rash occurs.
- Keep out of reach of children. If product is swallowed, get medical help or contact a Poison Control Center right away.

INDICATIONS AND USAGE

- Helps prevent sunburn

Keep out of reach of children. If product is swallowed, get medical help or contact a Poison Control Center right away.

PURPOSE

Sunscreen